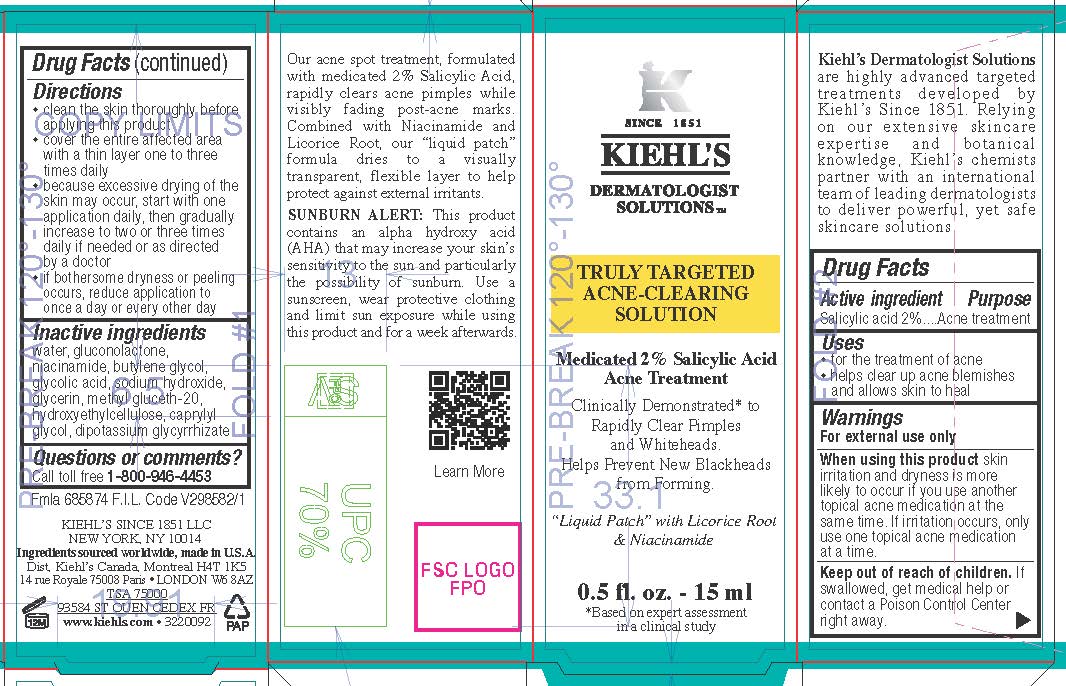 DRUG LABEL: Kiehls Since 1851 Dermatologist Solutions Truly Targeted Acne Clearing Solution
NDC: 49967-055 | Form: LIQUID
Manufacturer: L'Oreal USA Products Inc
Category: otc | Type: HUMAN OTC DRUG LABEL
Date: 20231230

ACTIVE INGREDIENTS: SALICYLIC ACID 20 mg/1 mL
INACTIVE INGREDIENTS: WATER; GLUCONOLACTONE; NIACINAMIDE; BUTYLENE GLYCOL; GLYCOLIC ACID; SODIUM HYDROXIDE; GLYCERIN; METHYL GLUCETH-20; HYDROXYETHYL CELLULOSE, UNSPECIFIED; CAPRYLYL GLYCOL; GLYCYRRHIZINATE DIPOTASSIUM

Drug Facts

Active ingredient

Salicylic acid 2%

Purpose

Acne treatment

Use

- for the treatment of acne
- helps clear up acne blemishes and allows skin to heal

Warnings

For external use only

When using this product

skin irritation and dryness is more likely to occur if you use another topical acne medication at the same time. If irritation occurs, only use one topical acne medication at a time.

Keep out of reach of children.

If swallowed, get medical help or contact a Poison Control Center right away.

Directions

- clean the skin thoroughly before applying this product
- cover the entire affected area with a thin layer one to three times daily
- because excessive drying of the skin may occur, start with one application daily, then gradually ingrease to two or three times dialy if neded or as directed by a doctor
- if bothersome dryness or peeling occurs, reduce application to once a day or every other dayl

Inactive ingredients

water, gluconolactone, niacinamide, butylene glycol, glycolic acid, sodium hydroxide, glycerin, methyl gluceth-20, hydroxyethylcellulose, caprylyl glycol, dipotassium glycyrrhizate

Questions or comments?

Call toll-free 1-800-946-4453